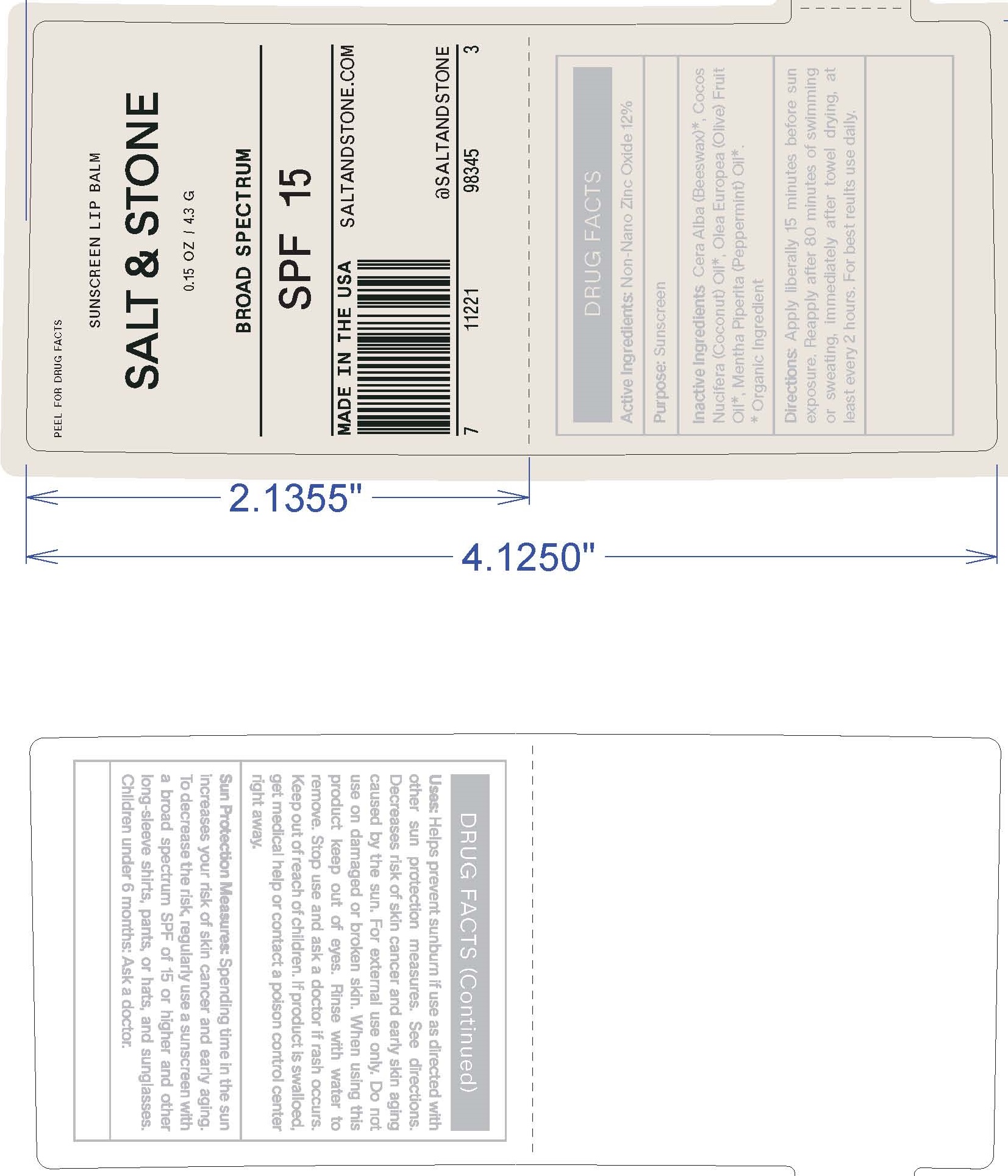 DRUG LABEL: ALL NATURAL LIP BALM
NDC: 71585-103 | Form: LOTION
Manufacturer: SALT AND STONE
Category: otc | Type: HUMAN OTC DRUG LABEL
Date: 20190411

ACTIVE INGREDIENTS: ZINC OXIDE 8 g/100 g
INACTIVE INGREDIENTS: ARGAN OIL; YELLOW WAX; BEHENYL BEHENATE; LEVOMENOL; SHEA BUTTER; CANDELILLA WAX; MEDIUM-CHAIN TRIGLYCERIDES; COCONUT OIL; CARNAUBA WAX; GLYCERYL CAPRYLATE; GLYCERYL 1-UNDECYLENATE; HYDROGENATED METHYL ABIETATE; ISOSTEARIC ACID; LECITHIN, SOYBEAN; POLYHYDROXYSTEARIC ACID (2300 MW); .ALPHA.-TOCOPHEROL ACETATE; POLYGLYCERYL-3 RICINOLEATE; CASTOR OIL; STEVIA LEAF; CORN OIL

SALT & STONE - ALL NATURAL LIP BALM SPF-30

ACTIVE INGREDIENTS

ZINC OXIDE 8%

PURPOSE

SUNSCREEN

USES

- HELPS PREVENT SUNBURN

WARNINGS

FOR EXTERNAL USE ONLY.

DO NOT USE ON DAMAGED OR BROKEN SKIN.

IF RASH OCCURS, DISCONTINUE USE AND CONSULT A HEALTH CARE PRACTITIONER. WHEN USING THIS PRODUCT: KEEP OUT OF EYES. RINSE WITH WATER TO REMOVE.

KEEP OUT OF REACH OF CHILDREN. IF PRODUCT IS SWALLOWED, GET MEDICAL HELP OR CONTACT A POISON CONTROL CENTER RIGHT AWAY.

DIRECTIONS

FOR USE ON CHILDREN LESS THAN 6 MONTHS OF AGE, CONSULT A HEALTH CARE PRACTITIONER. APPLY LIBERALLY/GENEROUSLY (AND EVENLY) 15 MINUTES BEFORE SUN EXPOSURE. REAPPLY AT LEAST EVERY 2 HOURS. REAPPLY AFTER 80 MINUTES OF SWIMMING OR SWEATING. REAPPLY IMMEDIATELY AFTER TOWEL DRYING.

SUN PROTECTIONS MEASURES: SPENDING TIME IN THE SUN INCREASES YOUR RISK OF SKIN CANCER AND EARLY SKIN AGING. TO DECREASE THIS RISK, REGULARLY USE A SUNSCREEN WITH A BROAD SPECTRUM SPF OF 15 OR HIGHER AND OTHER SUN PROTECTION MEASURES, INCLUDING LIMIT TIME IN THE SUN, ESPECIALLY FROM 10AM - 2PM, WEAR LONG-SLEEVED SHIRTS, PANTS, HATS AND SUNGLASSES.

INACTIVE INGREDIENTS

ARGANIA SPINOSA (ARGAN) KERNEL OIL, BEESWAX (CERA ALBA), BEHENYL BEHENATE, BISABOLOL, BUTYROSPERMUM PARKII (SHEA BUTTER), EUPHORBIA CERIFERA (CANDELILLA) WAX, CAPRYLIC/CAPRIC TRIGLYCERIDES, COCOS NUCIFERA (COCONUT) OIL, COPERNICIA CERIFERA (CARNAUBA) WAX, GLYCERYL CAPRYLATE, GLYCERYL UNDECYLENATE, HYDROGENATED METHYL ABIETATE, ISOSTEARIC ACID, LECITHIN, POLYHYDROXYSTEARIC ACID, POLYGLYCERYL-3 POLYRICINOLEATE, RICINUS COMMUNIS (CASTOR) SEED OIL, STEAIA REBAUDIANA, TOCOPHERYL ACETATE, VEGETABLE OIL.

OTHER INFORMATION

- PROTECT THIS PRODUCT FROM EXCESSIVE HEAT AND DIRECT SUN